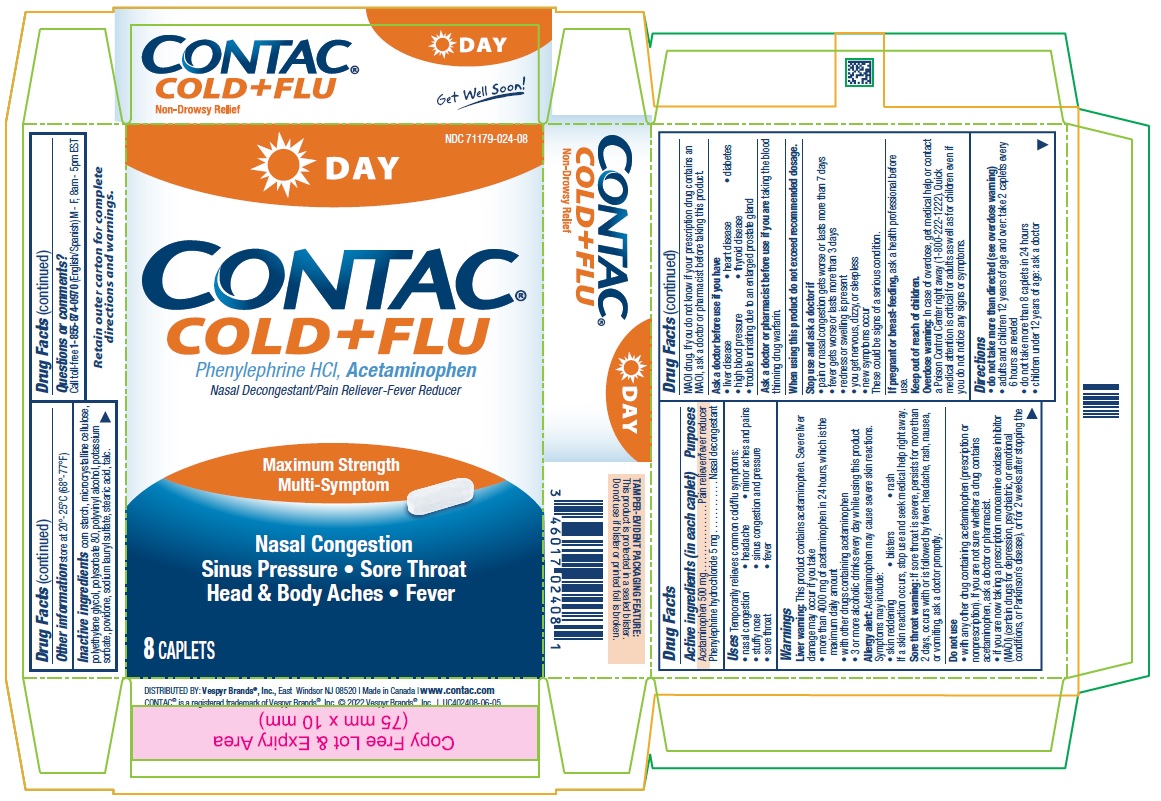 DRUG LABEL: CONTAC
NDC: 71179-024 | Form: TABLET
Manufacturer: Vespyr Brands, Inc.
Category: otc | Type: HUMAN OTC DRUG LABEL
Date: 20240101

ACTIVE INGREDIENTS: ACETAMINOPHEN 500 mg/1 1; PHENYLEPHRINE HYDROCHLORIDE 5 mg/1 1
INACTIVE INGREDIENTS: POLYVINYL ALCOHOL, UNSPECIFIED; STEARIC ACID; MICROCRYSTALLINE CELLULOSE; POLYETHYLENE GLYCOL, UNSPECIFIED; POVIDONE; POLYSORBATE 80; POTASSIUM SORBATE; SODIUM LAURYL SULFATE; STARCH, CORN; TALC

CONTAC Cold + Flu Day

Active ingredients (in each caplet)

Acetaminophen 500 mg
Phenylephrine hydrochloride 5 mg

Purposes

Pain reliever/fever reducer
Nasal decongestant

Uses

Temporarily relieves common cold/flu symptoms:
• nasal congestion • headache • minor aches and pains
• stuffy nose • sinus congestion and pressure
• sore throat • fever

Warnings

Liver warning: This product contains acetaminophen. Severe liver damage may occur if you take
• more than 4000 mg of acetaminophen in 24 hours, which is the maximum daily amount
• with other drugs containing acetaminophen
• 3 or more alcoholic drinks every day while using this product
Allergy alert: Acetaminophen may cause severe skin reactions. Symptoms may include:
• skin reddening • blisters • rash
If a skin reaction occurs, stop use and seek medical help right away.
Sore throat warning: If sore throat is severe, persists for more than 2 days, occurs with or is followed by fever, headache, rash, nausea, or vomiting, ask a doctor promptly.

Do not use
• with any other drug containing acetaminophen (prescription or nonprescription). If you are not sure whether a drug contains acetaminophen, ask a doctor or pharmacist.
• if you are now taking a prescription monoamine oxidase inhibitor (MAOI) (certain drugs for depression, psychiatric, or emotional
conditions, or Parkinson’s disease), or for 2 weeks after stopping the MAOI drug. If you do not know if your prescription drug contains an MAOI, ask a doctor or pharmacist before taking this product.

Ask a doctor before use if you have
• liver disease • heart disease • diabetes
• high blood pressure • thyroid disease
• trouble urinating due to an enlarged prostate gland

Ask a doctor or pharmacist before use if you are taking the blood thinning drug warfarin.

When using this product do not exceed recommended dosage.

Stop use and ask a doctor if
• pain or nasal congestion gets worse or lasts more than 7 days
• fever gets worse or lasts more than 3 days
• redness or swelling is present
• you get nervous, dizzy, or sleepless
• new symptoms occur
These could be signs of a serious condition.

PREGNANCY OR BREAST FEEDING

If pregnant or breast-feeding, ask a health professional before use.

Keep out of reach of children.

OVERDOSAGE

Overdose warning: In case of overdose, get medical help or contact a Poison Control Center right away (1-800-222-1222). Quick
medical attention is critical for adults as well as for children even if you do not notice any signs or symptoms.

Directions

• do not take more than directed (see overdose warning)
• adults and children 12 years of age and over: take 2 caplets every
6 hours as needed
• do not take more than 8 caplets in 24 hours
• children under 12 years of age: ask a doctor

Other information

store at 20°-25°C (68°-77°F)

Inactive ingredients

corn starch, microcrystalline cellulose, polyethylene glycol, polysorbate 80, polyvinyl alcohol, potassium sorbate, povidone, sodium lauryl sulfate, stearic acid, talc.

Questions or comments?

Call toll-free 1-855-874-0970 (English/Spanish) M - F, 8am - 5pm EST

Retain outer carton for complete directions and warnings.

TAMPER-EVIDENT PACKAGING FEATURE: This product is protected in a sealed blister. Do not use if blister or printed foil is broken.

CONTAC®

COLD + FLU DAY

Non-Drowsy Relief

DISTRIBUTED BY: Vespyr Brands®, Inc., East Windsor NJ 08520 | Made in Canada | www.contac.com
CONTAC® is a registered trademark of Vespyr Brands®, Inc. © 2022 Vespyr Brands®, Inc. | UC402408-06-05

PACKAGE LABEL

CONTACT®
COLD + FLU DAY
Phenylephrine HCl, Acetaminophen
Nasal Decongestant/Pain Reliever-Fever ReducerMaximum Strength

Multi-Symptom

Nasal Congestion

Sinus Pressure • Sore Throad

Head & Body Aches • Fever

8 CAPLETS

NDC 71179-024-08

Maximum Strength

Multi-Symptom

Nasal Congestion

Sinus Pressure • Sore Throad

Head & Body Aches • Fever